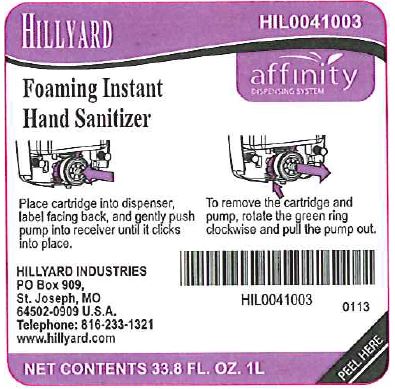 DRUG LABEL: Hillyard Foaming Instant Hand Sanitizer
NDC: 76402-410 | Form: LIQUID
Manufacturer: Hillyard GMP
Category: otc | Type: HUMAN OTC DRUG LABEL
Date: 20241230

ACTIVE INGREDIENTS: ALCOHOL 62 mL/100 mL
INACTIVE INGREDIENTS: WATER; PEG-10 DIMETHICONE (600 CST); GLYCERIN; ANHYDROUS CITRIC ACID; .ALPHA.-TOCOPHEROL; ALOE VERA LEAF

Hillyard Foaming Instant Hand Sanitizer

Active Ingredients

Ethyl Alcohol 62.0% w/w

Purpose

Antimicrobial

Uses

- For hand sanitizing to decrease bacteria on the skin.
- Recommended for repeated use.

Warnings – For External Use Only.

Flammable. Keep away from fire or flame.

When using this product

avoid contact with eyes. In case of eye contact, flush eyes thoroughly with water.

Stop use and ask a doctor if

irritation or redness develops, or if condition persists for more than 72 hours.

Keep out of reach of children.

If swallowed, get medical help or contact a Poison Control Center right away.

Directions

- Pump enough foam into palm of hand to cover both hands.
- Rub thoroughly over all surfaces of both hands.
- Rub hands together briskly until dry.
- Children under 6 years of age should be supervised when using this product.

Inactive Ingredients:

Water, PEG-10 Dimethicone, Glycerine, Fragrance, Citric Acid, Vitamin E, Aloe Barbadensis Leaf Juice.

Package/Label Principal Display Panel

Hillyard
Foaming Instant Hand Sanitizer

HIL0041003

Affinity
Dispensing System

Place cartridge into dispenser, label facing back, and gently push pump into receiver until it clicks into place.

To remove the cartridge and pump, rotate the green ring clockwise and pull the pump out.

HILLYARD INDUSTRIES
PO Box 909,
St. Joseph, MO
64502-0909 U.S.A.
Telephone: 816-233-1321
www.hillyard.com

NET CONTENTS 33.8 FL. OZ. 1L

Label